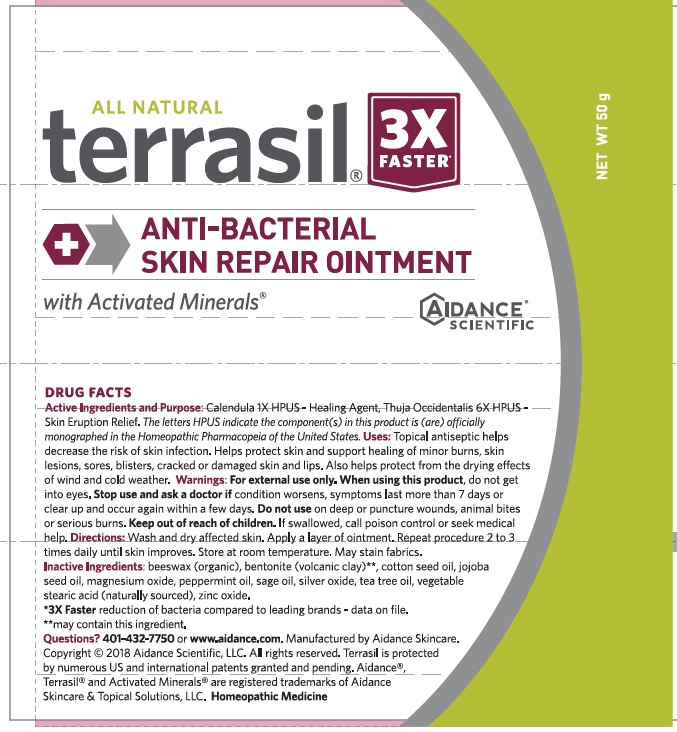 DRUG LABEL: Terrasil SKIN REPAIR
NDC: 24909-180 | Form: OINTMENT
Manufacturer: Aidance Skincare & Topical Solutions, LLC
Category: homeopathic | Type: HUMAN OTC DRUG LABEL
Date: 20240524

ACTIVE INGREDIENTS: CALENDULA OFFICINALIS FLOWER 1 [hp_X]/1 g; THUJA OCCIDENTALIS WHOLE 6 [hp_X]/1 g
INACTIVE INGREDIENTS: BENTONITE; COTTONSEED OIL; JOJOBA OIL; MAGNESIUM OXIDE; PEPPERMINT OIL; SAGE OIL; SILVER OXIDE; STEARIC ACID; TEA TREE OIL; WHITE WAX; ZINC OXIDE

24909-180 terrasil Skin Repair Ointment

Active Ingredients

Calendula 1X HPUS

Thuja Occidentalis 6X HPUS

The letters HPUS indicate the component(s) in this product is (are) officially monographed in the Homeopathic Pharmacopeia of the United States.

Purpose

Calendula – Healing Agent
Thuja Occidentalis – Skin Eruption Relief

Uses

- Topical antiseptic helps decrease the risk of skin infection. Helps protect skin and supports healing of minor burns, skin lesions, sores, blisters, cracked or damaged skin and lips.
- Also helps protect from the drying effects of wind and cold weather.

Warnings

For external use only. When using this product, do not get into eyes. Stop use and ask a doctor ifcondition worsens, symptoms last more than 7 days or clear up and occur again within a few days.

Do not useon deep or puncture wounds, animal bites or serious burns.

Keep out of reach of children. If swallowed, call poison control or seek medical help.

Directions

Wash and dry affected skin. Apply a layer of ointment. Repeat procedure 2 to 3 times daily until skin improves. Store at room temperature. May stain fabrics.

Inactive Ingredients

beeswax (organic), bentonite (volcanic clay)**, cotton seed oil, jojoba seed oil, magnesium oxide, peppermint oil, sage oil, silver oxide, tea tree oil, vegetable stearic acid (naturally sourced), zinc oxide.

**may contant this ingredient.

PRINCIPAL DISPLAY PANEL

All Natural
terrasil®
ANTI-BACTERIAL
SKIN REPAIR OINTMENT
with Activated Minerals®